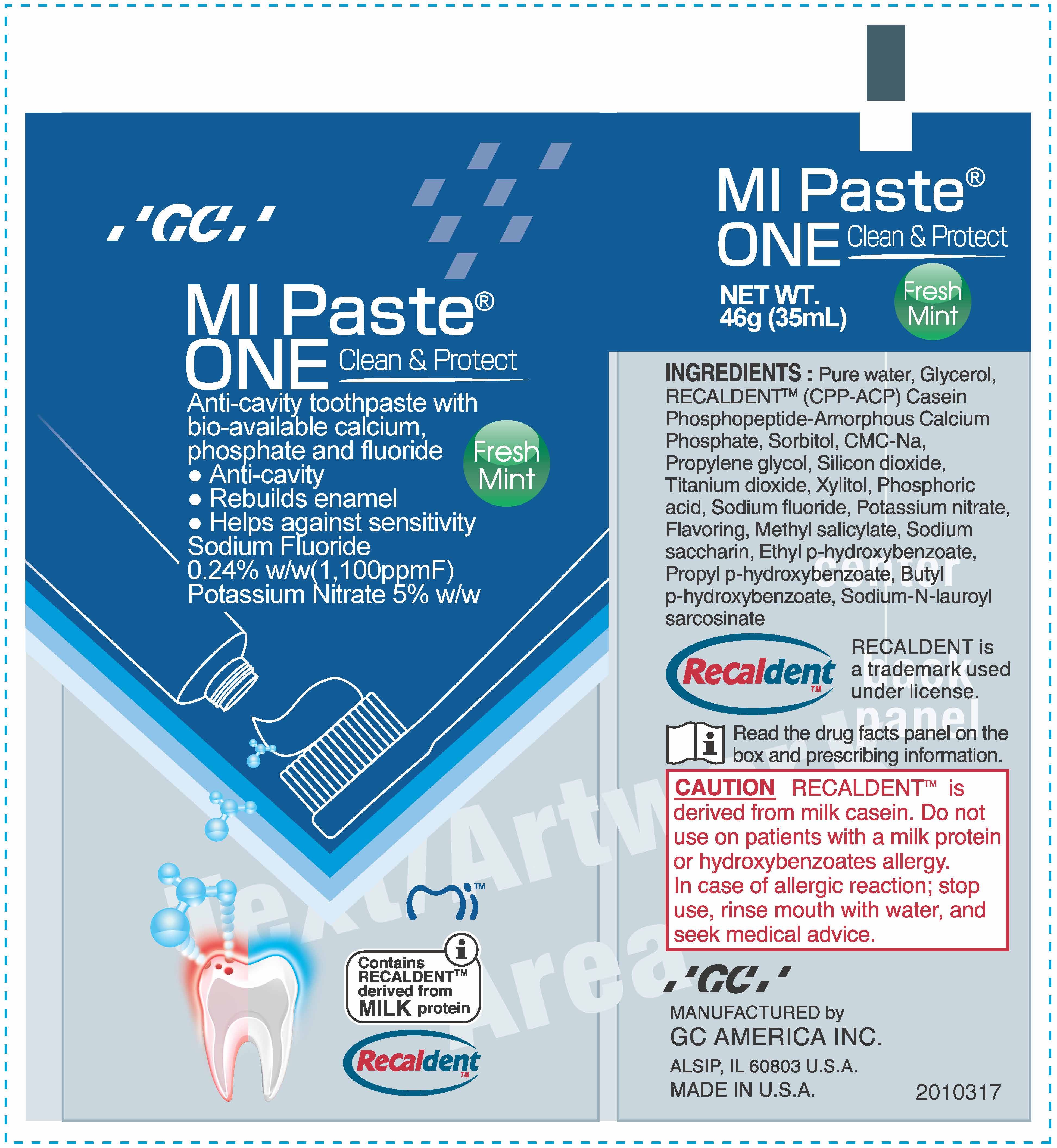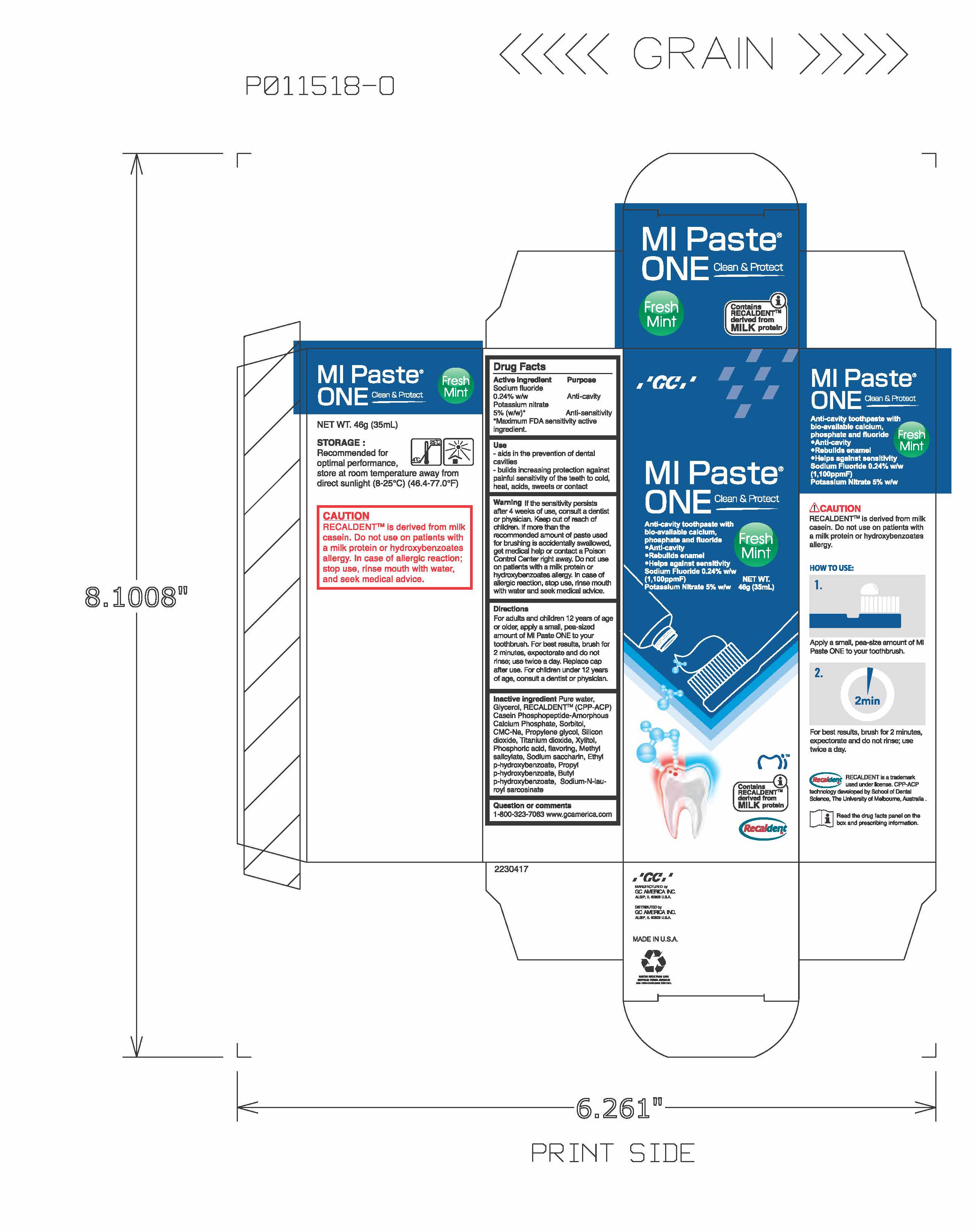 DRUG LABEL: MIPaste
NDC: 61596-437 | Form: PASTE, DENTIFRICE
Manufacturer: GC America Inc.
Category: otc | Type: HUMAN OTC DRUG LABEL
Date: 20201013

ACTIVE INGREDIENTS: SODIUM FLUORIDE 0.0024 g/1 g; POTASSIUM NITRATE 0.06 g/1 g
INACTIVE INGREDIENTS: SILICON DIOXIDE; SORBITOL; PROPYLENE GLYCOL; XYLITOL; PHOSPHORIC ACID; TITANIUM DIOXIDE; ETHYLPARABEN; BUTYLPARABEN; SACCHARIN SODIUM; PROPYLPARABEN; WATER; GLYCERIN; SODIUM LAUROYL SARCOSINATE; METHYL SALICYLATE; CALCIUM PHOSPHATE; CARBOXYMETHYLCELLULOSE SODIUM, UNSPECIFIED FORM

Active Ingredient

Sodium fluoride

0.24% w/w Anti-cavity

Potassium nitrate

5% (w/w)* Anti-sensitivity

*Maximum FDA sensitivity active ingredient

Use

-aids in the prevention of dental cavities

-builds increasing protection against painful sensitivity of the teeth to cold, heat, acids, sweets or contact

Warning

Warning If the sensitivity persists after 4 weeks of use, consult a dentist or physician. Keep out of reach of children. If more than the recommended amount of paste used for brushing is accidentally swallowed, get medical help or contact a Poison Control Center right away. Do not use on patients with a milk protein and/or hydroxybenzoates allergy. In case of allergic reaction, stop use, rinse mouth with water and seek medical advice.

Directions

For adults and children 12 years of age or older, apply a small, pea-sized amount of MI Paste One to your toothbrush. For best results, brush for 2 minutes, expectorate and do not rinse; use twice a day. Replace cap after use. For children under 12 years of age, consult a dentist or physician.

Inactive ingredient

Pure water, Glycerol, RECALDENTTM (CPP-ACP) Casein Phosphopeptide-Amorphous Calcium Phosphate, Sorbitol, CMC-Na, Propylene glycol, Silicon dioxide, Titanium dioxide, Xylitol, Phosphoric acid, flavoring, Methyl salicylate, Sodium saccharin, Ethyl p-hydroxybenzoate, Propyl p-hydroxybenzoate, Butyl p-hydroxybenzoate, Sodium-N-lauroyl sarcosinate

Question or comments

1-708-323-7063 www.gcamerica.com

Warning

Keep out of reach of children.

PURPOSE

Anti-cavity toothpaste with bio-available calcium.

Anti-cavity

Rebuilds enamel

Helps against sensitivity

Sodium Fluoride 0.24% w/w (1,100ppmF)

Potassium Nitrate 5% w/w/